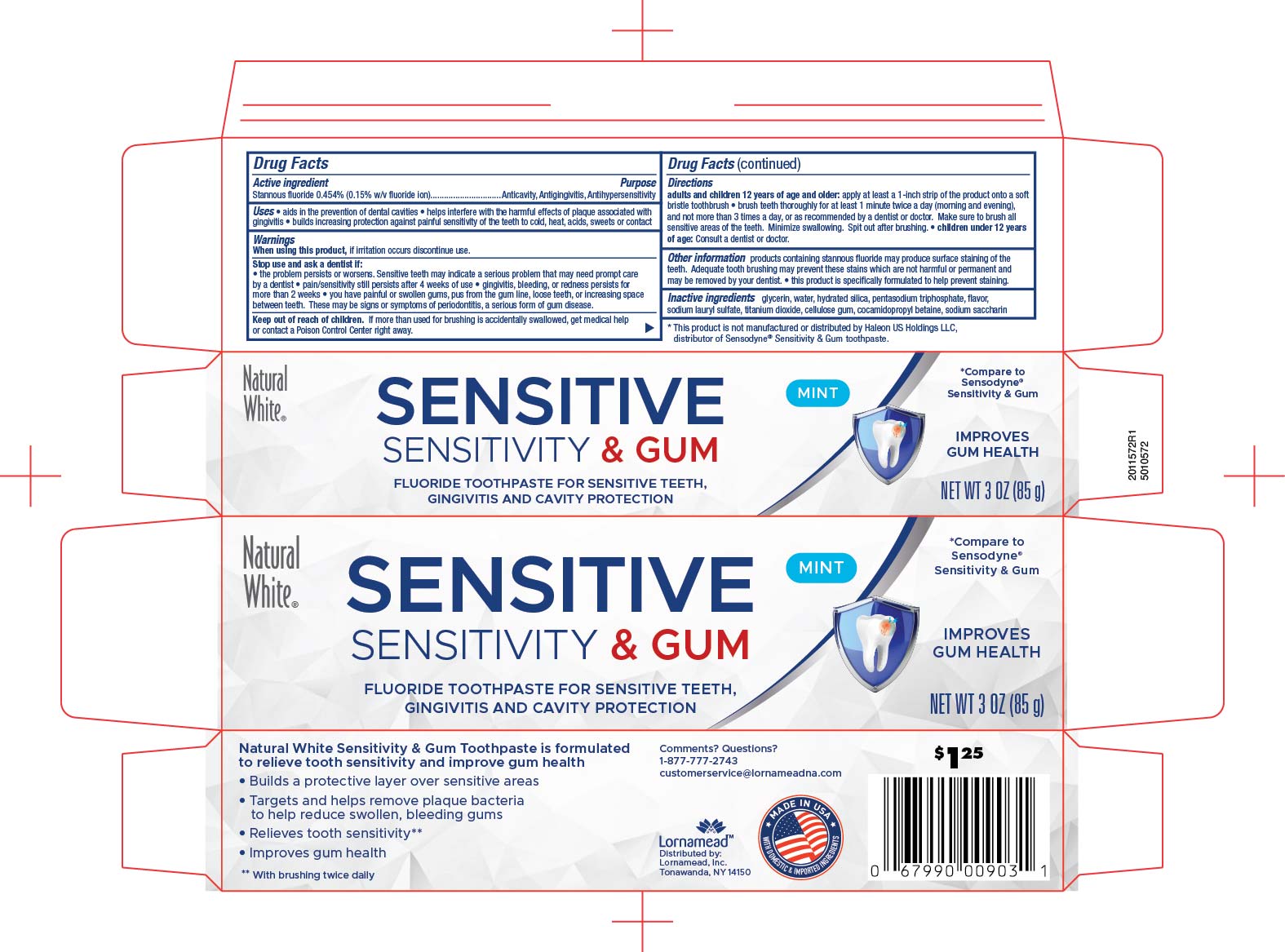 DRUG LABEL: Natural White Sensitivity and Gum
NDC: 62721-0003 | Form: PASTE, DENTIFRICE
Manufacturer: Lornamead Products
Category: otc | Type: HUMAN OTC DRUG LABEL
Date: 20251114

ACTIVE INGREDIENTS: STANNOUS FLUORIDE 0.15 g/100 g
INACTIVE INGREDIENTS: WATER; SODIUM LAURYL SULFATE; GLYCERIN; SODIUM TRIPOLYPHOSPHATE ANHYDROUS; COCAMIDOPROPYL BETAINE; HYDRATED SILICA; TITANIUM DIOXIDE; CARBOXYMETHYLCELLULOSE SODIUM; SODIUM SACCHARIN

5010572 Dollar Tree NW Sensitive & Gum TP (8015053)

ACTIVE INGREDIENT

Stannous fluoride 0.454% (0.15% w/v fluoride ion)

PURPOSE

Anticavity, Antigingivitis, Antihypersensitivity

PURPOSE

- aids in the prevention of dental cavities
- helps interfere with the harmful effects of plaque associated with gingivitis
- builds increasing protection against painful sensitivity of the teeth to cold, heat, acids, sweets or contact

WARNINGS

When using this product, if irritation occurs discontinue use.

Stop use and ask a dentist if:

- the problem persists or worsens. Sensitive teeths may indicate a serious problem that may need prompt care by a dentist
- pain/sensitivity still persists after 4 weeks of use
- gingivitis, bleeding, or redness persists formore that 2 weeks
- you have painful or swollen gums,pus from the gum line, loose teeth, or increasinf space between teeth. These may be signs or symptoms of periodontitis, a serious form of gum disease.

keep out of reach of children. If more than used for brushing is accidentally swallowed, get medical help or contact a Poison Control Center right away.

Directions

adults and children 12 years of age and older: apply at least 1-inch strip of the product onto a soft bristle toothbrush

- brush teeth thoroughly for at least 1 minute twice a day (morning and evening), and not more than 3 times a day, or as recommended by a dentist or doctor. make sure to brush all sensitive areas of the teeth. Minimize swallowing. Spit out after brushing.
- children under 12 years of age: Consult a dentist or doctor.

Other information products containing stannous fluoride may produce surface staining of the teeth. Adequate tooth brushing may prevent these stains which are not harmful or permanent and may be removed by your dentist.

- this product is specifically formulated to help prevent staining.

INACTIVE INGREDIENT

Inactive ingredients glycerin, water, hydrated silica pentasodium triphosphate, flavor, sodium lauryl sulfate, titanium dioxide, cellulose gum, cocamidopropyl betaine, sodium saccharin

Directions

adults and children 12 years of age and older: apply at least 1-inch strip of the product onto a soft bristle toothbrush

brush teeth thoroughly for at least 1 minute twice a day (morning and evening), and not more than 3 times a day, or as recommended by a dentist or doctor. make sure to brush all sensitive areas of the teeth. Minimize swallowing. Spit out after brushing.

- children under 12 years of age: Consult a dentist or doctor.